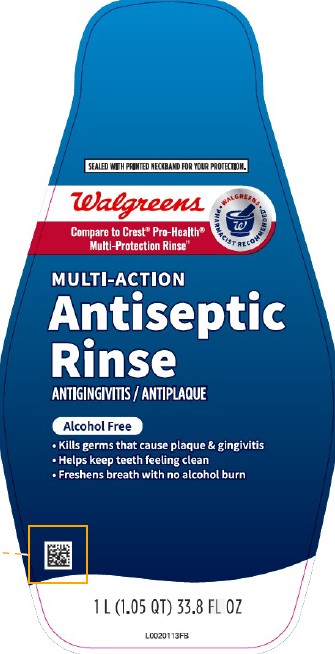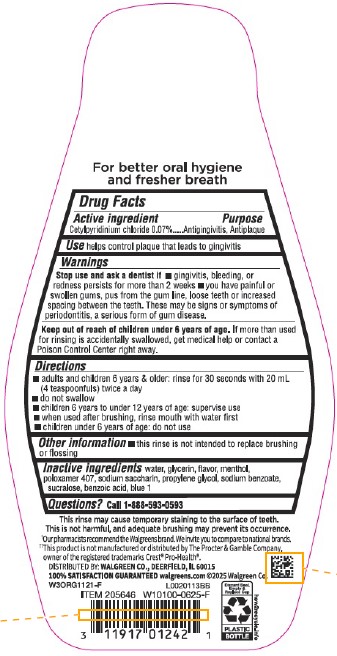 DRUG LABEL: Health
NDC: 0363-0099 | Form: MOUTHWASH
Manufacturer: Walgreen Co.
Category: otc | Type: HUMAN OTC DRUG LABEL
Date: 20260212

ACTIVE INGREDIENTS: CETYLPYRIDINIUM CHLORIDE 0.7 mg/1 mL
INACTIVE INGREDIENTS: WATER; GLYCERIN; MENTHOL, UNSPECIFIED FORM; POLOXAMER 407; SACCHARIN SODIUM; PROPYLENE GLYCOL; SODIUM BENZOATE; SUCRALOSE; BENZOIC ACID; FD&C BLUE NO. 1

Walgreens 299.006/299AM
Multi Action Alcohol Free Antiseptic Rinse w/CPC

Claims

For better oral hygiene and fresher breath

Active ingredient

Cetylpyridinium chloride 0.07%

Purpose

Antigingivitis, Antiplaque

Use

helps control plaque that leads to gingivitis

Warnings

For this product

Stop Use and ask a dentist if

- gingivitis, bleeding, or redness persists for more than 2 weeks
- you have painful or swollen gums, pus from the gum line, loose teeth or increased spacing between the teeth. These may be signs or symptoms of periodontitis, a serious form of gum disease.

Keep out of reach of children under 6 years of age.

If more than used for rinsing is accidentally swallowed, get medical help or contact a Poison Control Center right away.

Directions

- adults and children 6 years & older: rinse for 30 seconds with 20 mL (4 teaspoonfuls) twice a day
- do not swallow
- children 6 years to under 12 years of age: supervise use
- when used after brushing, rinse mouth with water first
- children under 6 years of age: do not use

Other information

- this rinse is not intended to replace brushing or flossing

Inactive ingredients

water, glycerin, flavor, menthol, poloxamer 407, sodium saccharin, propylene glycol, sodium benzoate, sucralose, benzoic acid, blue 1

Questions?

Call 1-888-593-0593

Disclaimers

This rinse may cause temporary staining to the surface of teeth.

This is not harmful, and adequate brushing may prevent its occurence.

†Our pharmacists recommend the Walgreens brand. We invite you to compare to national brands.

††This product is not manufactured or distributed by The Procter & Gamble Company, owner of the registered trademarks Crest®and Pro-Health.

Adverse reaction

DISTRIBUTED BY: WALGREEN CO., DEERFIELD, IL 60015

100% SATISFACTION GUARANTEED walgreens.com ©2025 Walgreen Co.

Discard Seal, Empty & Replace Cap

PLASTIC BOTTLE

how2recycle.info

Principal display panel

SEALED WITH PRINTED NECKBAND FOR YOUR PROTECTION.

Walgreens

Compare to Crest® Pro-Health®Multi-Protection Rinse††

WALGREENS PHARMACIST RECOMMENDED

MULTI-ACTION

Antiseptic Rinse

ANTIGINGIVITIS / ANTIPLAQUE

Alcohol free

- Kills germs that cause plaque & gingivitis
- Helps keep teeth feeling clean
- Freshens breath with no alcohol burns

1 L (1.05 QT) 33.8 FL OZ